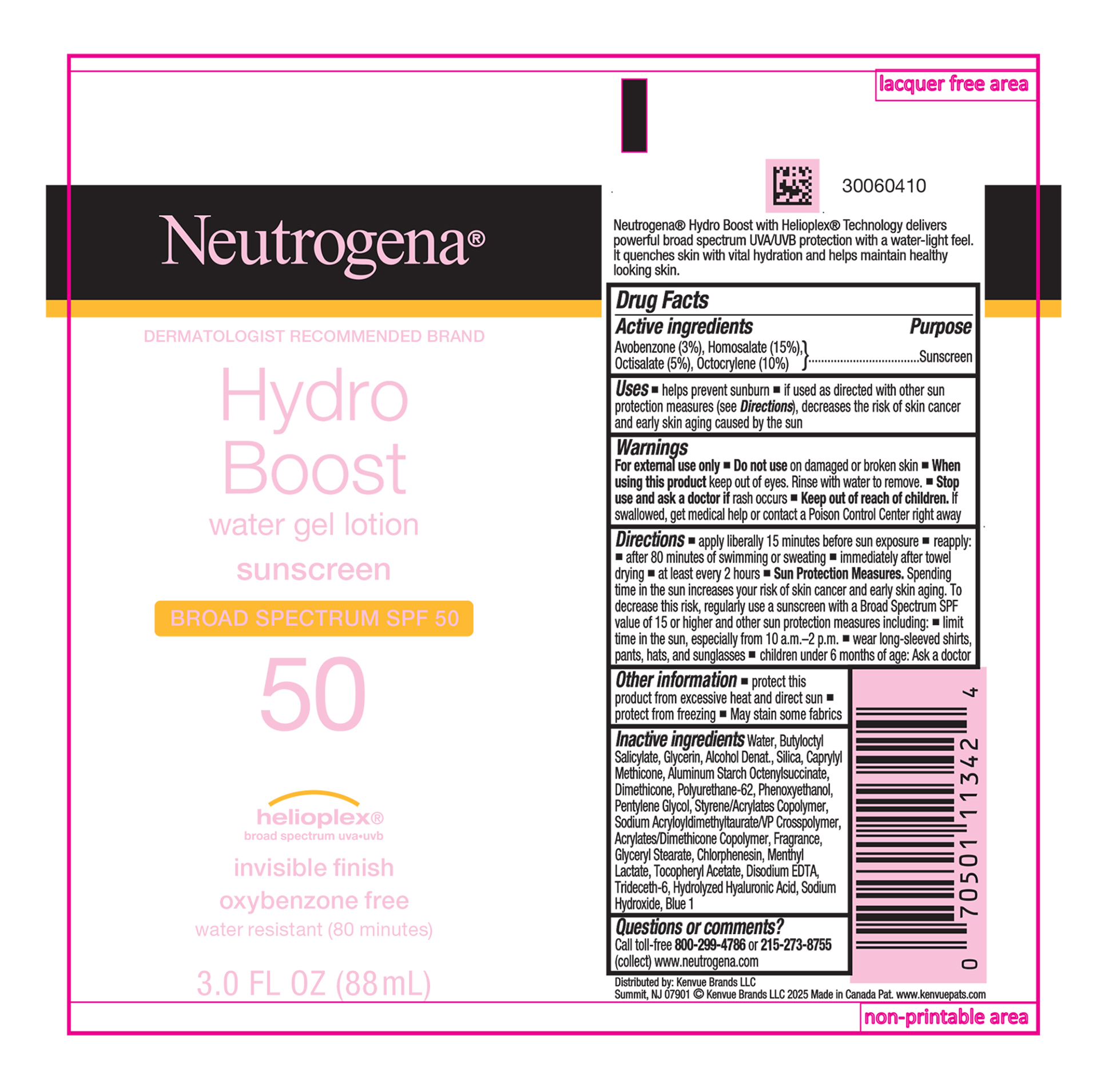 DRUG LABEL: Neutrogena Hydro Boost Water Gel Sunscreen Broad Spectrum SPF 50
NDC: 69968-0669 | Form: LOTION
Manufacturer: Kenvue Brands LLC
Category: otc | Type: HUMAN OTC DRUG LABEL
Date: 20251106

ACTIVE INGREDIENTS: AVOBENZONE 30 mg/1 mL; HOMOSALATE 150 mg/1 mL; OCTISALATE 50 mg/1 mL; OCTOCRYLENE 100 mg/1 mL
INACTIVE INGREDIENTS: HYALURONIC ACID; POLYURETHANE-62; GLYCERIN; ALCOHOL; BUTYLOCTYL SALICYLATE; SILICON DIOXIDE; CAPRYLYL TRISILOXANE; ALUMINUM STARCH OCTENYLSUCCINATE; DIMETHICONE; PHENOXYETHANOL; PENTYLENE GLYCOL; BUTYL METHACRYLATE/METHYL METHACRYLATE/METHACRYLIC ACID/STYRENE CROSSPOLYMER; GLYCERYL MONOSTEARATE; CHLORPHENESIN; MENTHYL LACTATE, (-)-; .ALPHA.-TOCOPHEROL ACETATE; EDETATE DISODIUM; TRIDECETH-6; SODIUM HYDROXIDE; FD&C BLUE NO. 1; WATER; 2-ETHYLHEXYL ACRYLATE, METHACRYLATE, METHYL METHACRYLATE, OR BUTYL METHACRYLATE/HYDROXYPROPYL DIMETHICONE COPOLYMER (30000-300000 MW)

Neutrogena® Hydro Boost water gel sunscreen BROAD SPECTRUM SPF 50

Drug Facts

ACTIVE INGREDIENT

Active Ingredients | Purpose
Avobenzone 3% | Sunscreen
Homosalate 15% | Sunscreen
Octisalate 5% | Sunscreen
Octocrylene 10% | Sunscreen

Uses

- Helps prevent sunburn
- if used as directed with other sun protection measures (see Directions), decreases the risk of skin cancer and early skin aging caused by the sun

Warnings

For external use only

- Do not use on damaged or broken skin

- When using this product keep out of eyes. Rinse with water to remove.

- Stop use and ask a doctor if rash occurs

- Keep out of reach of children. If swallowed, get medical help or contact a Poison Control Center right away.

Directions

- apply liberally 15 minutes before sun exposure
  - reapply:
    - after 80 minutes of swimming or sweating
    - immediately after towel drying
    - at least every 2 hours
- Sun Protection Measures. Spending time in the sun increases your risk of skin cancer and early skin aging. To decrease this risk, regularly use a sunscreen with a broad spectrum SPF value of 15 or higher and other sun protection measures including:
  - limit time in the sun, especially from 10 a.m.-2 p.m.
  - wear long-sleeved shirts, pants, hats, and sunglasses
  - children under 6 months of age: Ask a doctor

Other information

- protect this product from excessive heat and direct sun
- protect from freezing
- May stain some fabrics

Inactive ingredients

Water, Butyloctyl Salicylate, Glycerin, Alcohol Denat., Silica, Caprylyl Methicone, Aluminum Starch Octenylsuccinate, Dimethicone, Polyurethane-62, Phenoxyethanol, Pentylene Glycol, Styrene/Acrylates Copolymer, Sodium Acryloyldimethyltaurate/VP Crosspolymer, Acrylates/Dimethicone Copolymer, Fragrance, Glyceryl Stearate, Chlorphenesin, Menthyl Lactate, Tocopheryl Acetate, Disodium EDTA, Trideceth-6, Hydrolyzed Hyaluronic Acid, Sodium Hydroxide, Blue 1

Questions or comments?

Call toll-free 800-299-4786 or 215-273-8755 (collect) www.neutrogena.com

Distributed by:

Kenvue Brands LLC

Summit, NJ 07901

PRINCIPAL DISPLAY PANEL - 88 mL Tube Label

Neutrogena®

DERMATOLOGIST RECOMMENDED BRAND
Hydro
Boost
water gel lotion
sunscreen
BROAD SPECTRUM SPF 50
50
helioplex®
broad spectrum uva.uvb
invisible finish
oxybenzone free
water resistant (80 minutes)
3.0 FL OZ (88 mL)